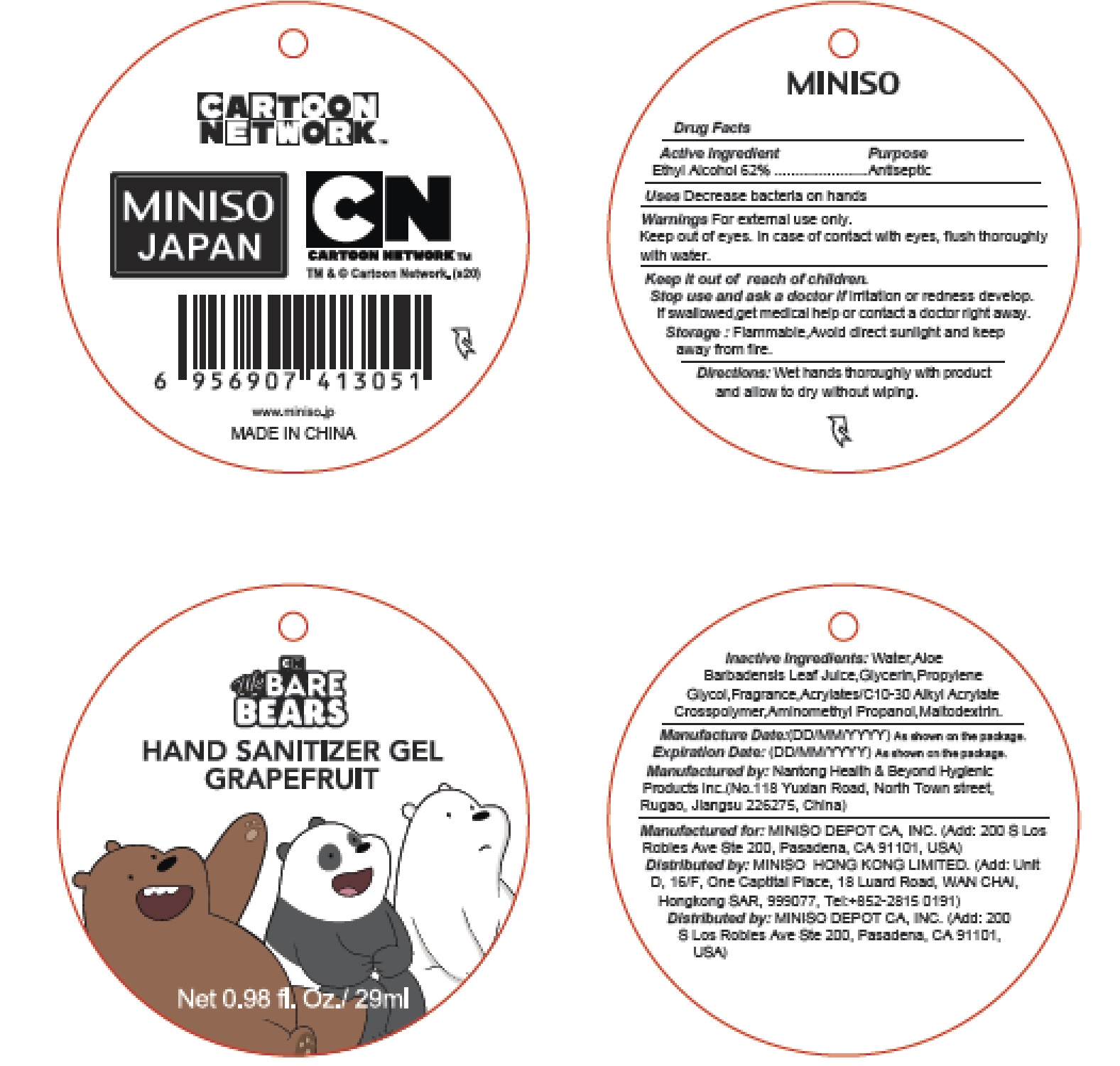 DRUG LABEL: Hand Sanitizer
NDC: 73950-005 | Form: GEL
Manufacturer: MINISO DEPOT CA, INC.
Category: otc | Type: HUMAN OTC DRUG LABEL
Date: 20200525

ACTIVE INGREDIENTS: ALCOHOL 62 mL/100 mL
INACTIVE INGREDIENTS: AMINOMETHYLPROPANOL; MALTODEXTRIN; ALOE VERA LEAF; PROPYLENE GLYCOL; WATER; GLYCERIN; CARBOMER INTERPOLYMER TYPE A (55000 CPS)

Active Ingredient
Ethyl Alcohol 62%

Purpose
Antiseptic

INDICATIONS AND USAGE

Uses Decrease bacteria on hands

Warnings For external use only.

Keep out of eyes. In case of contact with eyes, flush thoroughly with water.

Keep it out of reach of children.

Stop use and ask a doctor if irritation or redness develop.If swallowed,get medical help or contact a doctor right away.

STORAGE AND HANDLING

Storage: Flammable,Avoid direct sunlight and keep away from fire.

DOSAGE AND ADMINISTRATION

Directions: Wet hands thoroughly with product and allow to dry without wiping.

Inactive Ingredients:

Water, Aloe Barbadensis Leaf Juice, Glycerin, Propylene Glycol, Fragrance, Acrylates/C10-30 AlkyI Acrylate Crosspolymer, Aminomethyl Propanol, Maltodextrin.